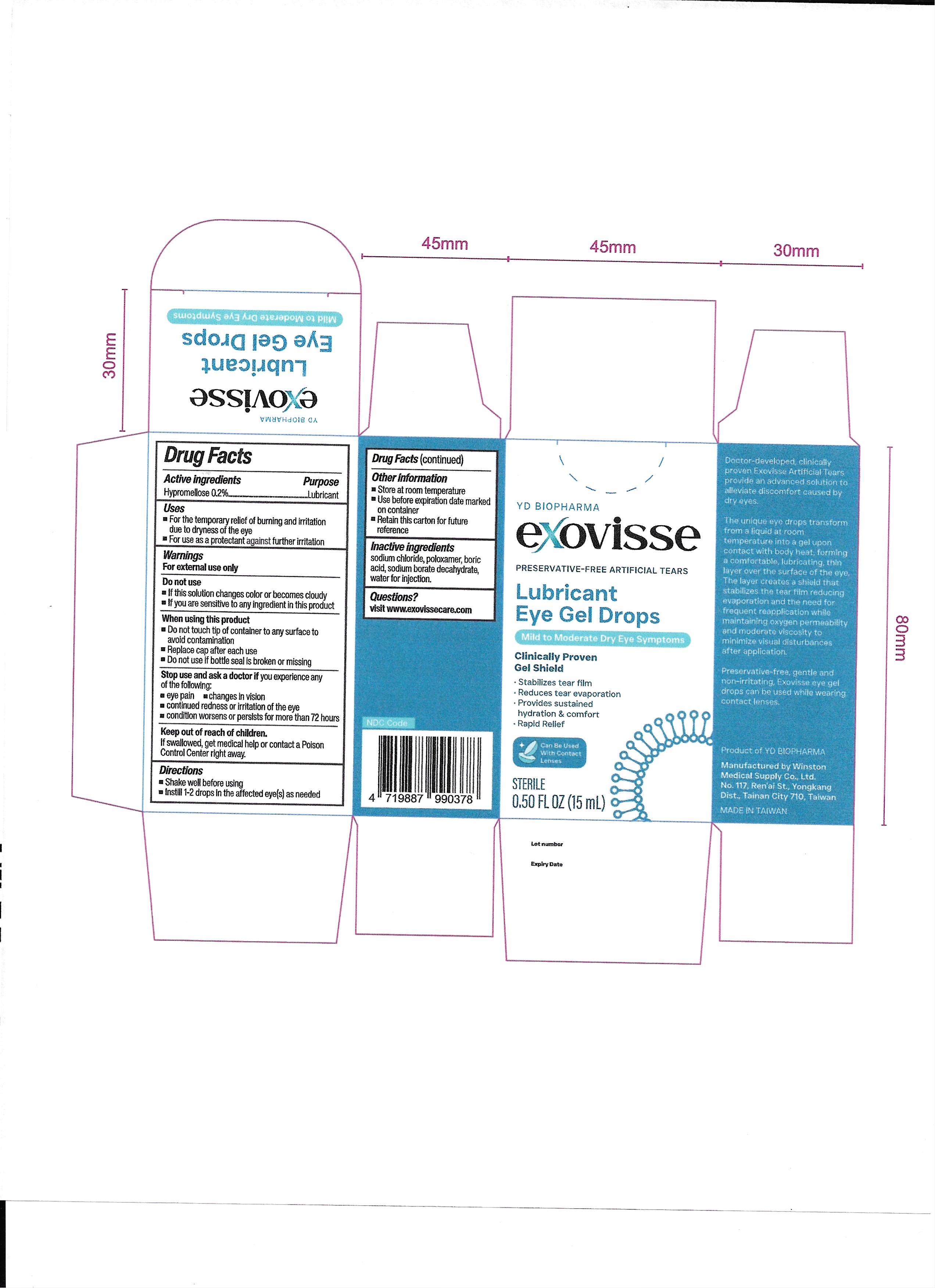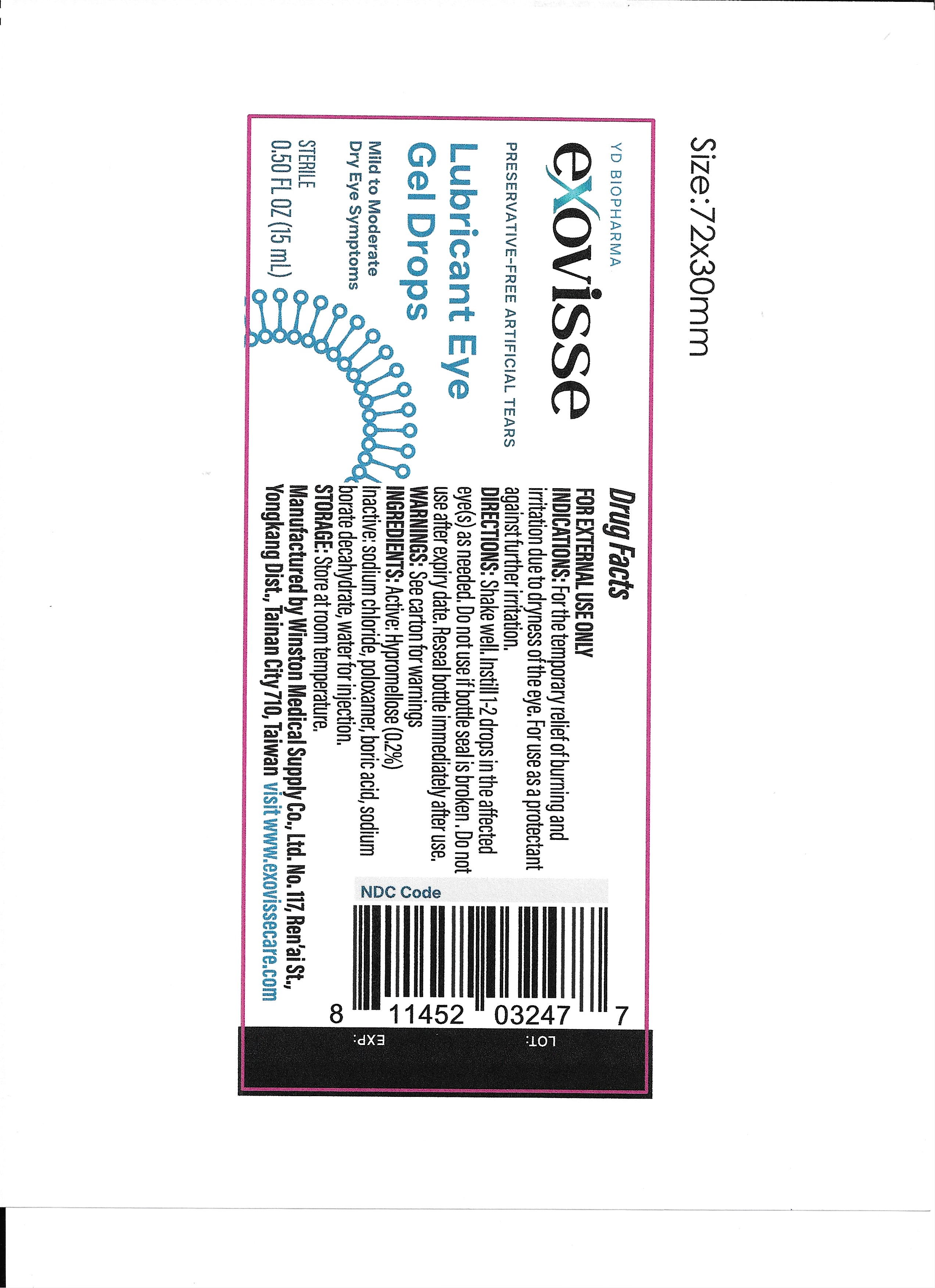 DRUG LABEL: Exovisse Preservative-Free Artificial Tears
NDC: 87106-002 | Form: GEL
Manufacturer: YD BIO USA, INC.
Category: otc | Type: HUMAN OTC DRUG LABEL
Date: 20250915

ACTIVE INGREDIENTS: HYPROMELLOSES 0.2 g/100 g
INACTIVE INGREDIENTS: SODIUM CHLORIDE; SODIUM BORATE; BORIC ACID; WATER; POLOXAMER 188

002-01

ACTIVE INGREDIENT

Hypromellose 0.2%

Stop use and ask a doctor if you experience any of the following:

Eye pain
Changes in vision
Continued redness or irritation of the eye
Condition worsens or persists for more than 72 hours

Do not use

If this solution changes color or becomes cloudy
If you are sensitive to any ingredient in this product

Keep out of reach of children.

If swallowed, get medical help or contact a Poison Control Center right away.

PURPOSE

Lubricant.

QUESTIONS

visit www.exovissecare.com

Stop use and ask a doctor if you experience any of the following:

Eye pain
Changes in vision
Continued redness or irritation of the eye
Condition worsens or persists for more than 72 hours

When using this product

Do not touch tip of container to any surface to avoid contamination
Replace cap after each use
Do not use if bottle seal is broken or missing

OTHER SAFETY INFORMATION

Store at room temperature
Use before expiration date marked on container
Retain this carton for future reference

DOSAGE AND ADMINISTRATION

Shake well before using
Instill 1-2 drops in the affected eye(s) as needed

WARNINGS

For external use only

INDICATIONS AND USAGE

For the temporary relief of burning and irritation due to dryness of the eye
For use as a protectant against further irritation

INACTIVE INGREDIENT

Sodium chloride, poloxamer, boric acid, sodium borate decahydrate, water for injection.